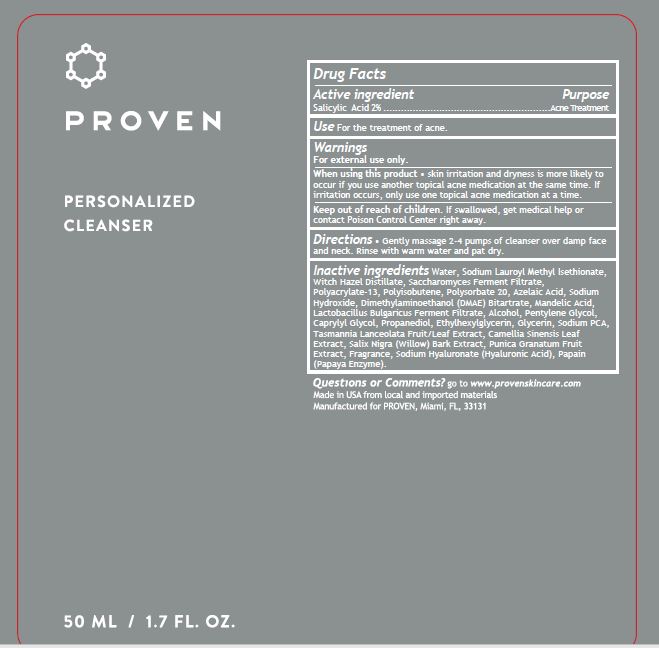 DRUG LABEL: Proven Acne Cleanser
NDC: 73572-010 | Form: CREAM
Manufacturer: Proven Skincare
Category: otc | Type: HUMAN OTC DRUG LABEL
Date: 20240101

ACTIVE INGREDIENTS: SALICYLIC ACID 2 g/100 g
INACTIVE INGREDIENTS: GLYCERIN; AZELAIC ACID; SODIUM HYDROXIDE; GREEN TEA LEAF; CAPRYLYL GLYCOL; ALCOHOL; ETHYLHEXYLGLYCERIN; FRAGRANCE 13576; PAPAIN; PENTYLENE GLYCOL; POLYISOBUTYLENE (55000 MW); TASMANNIA LANCEOLATA FRUIT; PHENOXYETHANOL; PROPANEDIOL; SODIUM HYALURONATE; YEAST; SODIUM PCA; SORBITAN ISOSTEARATE; LACTOBACILLUS DELBRUECKII BULGARICUS; WATER; DEANOL BITARTRATE; WITCH HAZEL; XANTHAN GUM; MANDELIC ACID; POLYACRYLATE-13; SODIUM CHLORIDE; SODIUM LAUROYL METHYL ISETHIONATE; EDETATE DISODIUM; POLYSORBATE 20; PUNICA GRANATUM ROOT BARK; SALIX ALBA BARK

Proven Personalized Cleanser

ACTIVE INGREDIENT

Salicylic Acid 2%

PURPOSE

Acne Treatment

INDICATIONS AND USAGE

Use For the treatment of acne.

Warnings

For external use only.

When using this product • skin irritation and dryness is more likely to
occur if you use another topical acne medication at the same time. If
irritation occurs, only use one topical acne medication at a time.

Keep out of reach of children. If swallowed, get medical help or
contact Poison Control Center right away.

DOSAGE AND ADMINISTRATION

Directions • Gently massage 2-4 pumps of cleanser over damp face
and neck. Rinse with warm water and pat dry.

INACTIVE INGREDIENT

Azelaic Acid

Camellia Sinensis Leaf Extract

Caprylyl Glycol

Disodium EDTA

DMAE Bitartrate

Ethanol

Ethylhexylglycerin

Fragrance

Glycerin

Lactobacillus Bulgaricus Ferment Filtrate

Mandelic Acid

Papain

Pentylene Glycol

Phenoxyethanol

Polyacrylate-13

Polyisobutene

Polysorbate 20

Propanediol

Punica Granatum Extract

Salix Alba (Willow) Bark Extract

Sodium Chloride

Sodium Hyaluronate

Sodium PCA

Sodium Hydroxide

Sodium Lauroyl Methyl Isethionate

Sorbitan isostearate

Tasmannia Lanceolata Fruit/Leaf Extract

Water

Witch Hazel Distillate

Xanthan Gum

Yeast Extract

QUESTIONS

go to www.provenskincare.com